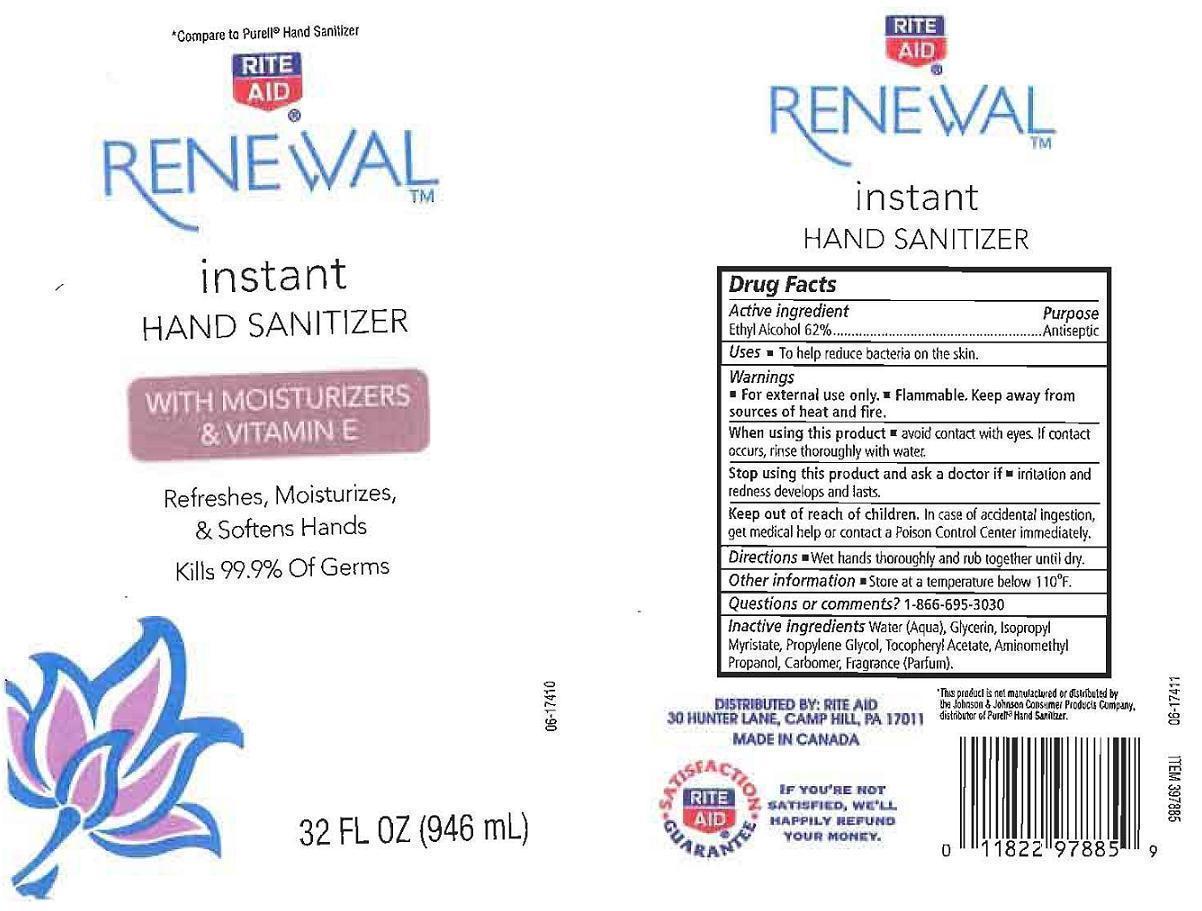 DRUG LABEL: RITE AID RENEWAL
NDC: 11822-2683 | Form: LIQUID
Manufacturer: RITE AID CORPORATION
Category: otc | Type: HUMAN OTC DRUG LABEL
Date: 20121001

ACTIVE INGREDIENTS: ALCOHOL 620 mg/1 mL
INACTIVE INGREDIENTS: WATER; GLYCERIN; ISOPROPYL MYRISTATE; PROPYLENE GLYCOL; .ALPHA.-TOCOPHEROL ACETATE; AMINOMETHYLPROPANOL; CARBOMER 934

DRUG FACTS

ACTIVE INGREDIENT

ETHYL ALCOHOL 62%

PURPOSE

ANTISEPTIC

USES

TO HELP REDUCE BACTERIA ON THE SKIN

WARNINGS

FOR EXTERNAL USE ONLY. FLAMMABLE. KEEP AWAY FROM SOURCES OF HEAT AND FIRE.

WHEN USING THIS PRODUCT

STOP USING THIS PRODUCT AND ASK A DOCTOR IF

KEEP OUT OF REACH OF CHILDREN

IN CASE OF ACCIDENTAL INGESTION, GET MEDICAL HELP OR CONTACT A POISON CONTROL CENTER IMMEDIATELY.

DIRECTIONS

WET HANDS THOROUGHLY AND RUN TOGETHER UNTIL DRY.

OTHER INFORMATION

STORE AT A TEMPERATURE BELOW 110F.

QUESTIONS OR COMMENTS?

1-866-695-3030

INACTIVE INGREDIENTS

WATER (AQUA), GLYCERIN, ISOPROPYL MYRISTATE, PROPYLENE GLYCOL, TOCOPHERYL ACETATE, AMINOMETHYL PROPANOL, CARBOMER, FRAGRANCE (PARFUM).